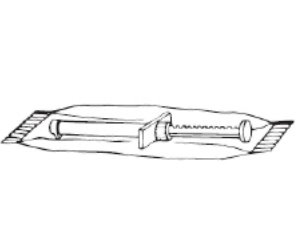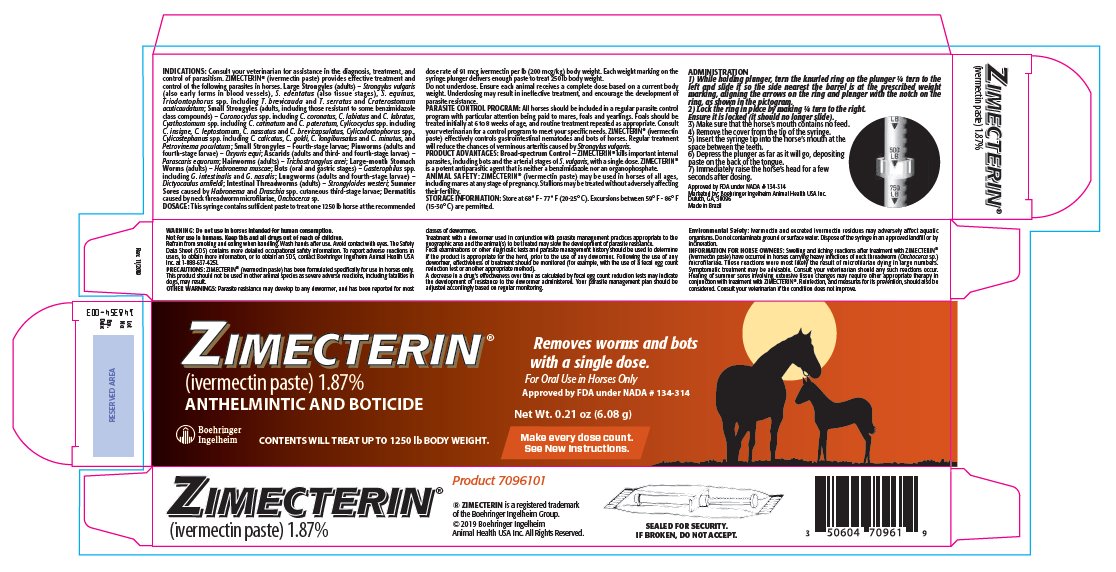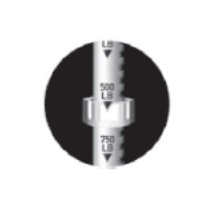 DRUG LABEL: ZIMECTERIN
NDC: 0010-7096 | Form: PASTE
Manufacturer: Boehringer Ingelheim Animal Health USA Inc.
Category: animal | Type: OTC ANIMAL DRUG LABEL
Date: 20240103

ACTIVE INGREDIENTS: ivermectin 18.7 mg/1 g

ZIMECTERIN®
(ivermectin paste) 1.87%

INDICATIONS:

Consult your veterinarian for assistance in the diagnosis, treatment, and control of parasitism. ZIMECTERIN® (ivermectin paste) provides effective treatment and control of the following parasites in horses. Large Strongyles (adults) – Strongylus vulgaris (also early forms in blood vessels), S. edentatus (also tissue stages), S. equinus, Triodontophorus spp. including T. brevicauda and T. serratus and Craterostomum acuticaudatum; Small Strongyles (adults, including those resistant to some benzimidazole class compounds) – Coronocyclus spp. including C. coronatus, C. labiatus and C. labratus, Cyathostomum spp. including C. catinatum and C. pateratum, Cylicocyclus spp. including C. insigne, C. leptostomum, C. nassatus and C. brevicapsulatus, Cylicodontophorus spp., Cylicostephanus spp. including C. calicatus, C. goldi, C. longibursatus and C. minutus, and Petrovinema poculatum; Small Strongyles – Fourth-stage larvae; Pinworms (adults and fourth-stage larvae) – Oxyuris equi; Ascarids (adults and third- and fourth-stage larvae) – Parascaris equorum; Hairworms (adults) – Trichostrongylus axei; Large-mouth Stomach Worms (adults) – Habronema muscae; Bots (oral and gastric stages) – Gasterophilus spp. including G. intestinalis and G. nasalis; Lungworms (adults and fourth-stage larvae) – Dictyocaulus arnfieldi; Intestinal Threadworms (adults) – Strongyloides westeri; Summer Sores caused by Habronema and Draschia spp. cutaneous third-stage larvae; Dermatitis caused by neck threadworm microfilariae, Onchocerca sp.

DOSAGE:

This syringe contains sufficient paste to treat one 1250 lb horse at the recommended dose rate of 91 mcg ivermectin per lb (200 mcg/kg) body weight. Each weight marking on the syringe plunger delivers enough paste to treat 250 lb body weight.

Do not underdose. Ensure each animal receives a complete dose based on a current body weight. Underdosing may result in ineffective treatment, and encourage the development of parasite resistance.

PARASITE CONTROL PROGRAM:

All horses should be included in a regular parasite control program with particular attention being paid to mares, foals and yearlings. Foals should be treated initially at 6 to 8 weeks of age, and routine treatment repeated as appropriate. Consult your veterinarian for a control program to meet your specific needs. ZIMECTERIN® (ivermectin paste) effectively controls gastrointestinal nematodes and bots of horses. Regular treatment will reduce the chances of verminous arteritis caused by Strongylus vulgaris.

PRODUCT ADVANTAGES:

Broad-spectrum Control – ZIMECTERIN® kills important internal parasites, including bots and the arterial stages of S. vulgaris, with a single dose. ZIMECTERIN® is a potent antiparasitic agent that is neither a benzimidazole nor an organophosphate.

STORAGE INFORMATION:

Store at 68° F - 77° F (20-25° C). Excursions between 59° F - 86° F (15-30° C) are permitted.

ADMINISTRATION:

1) While holding plunger, turn the knurled ring on the plunger ¼ turn to the left and slide it so the side nearest the barrel is at the prescribed weight marking, aligning the arrows on the ring and plunger with the notch on the ring, as shown in the pictogram.

2) Lock the ring in place by making ¼ turn to the right. Ensure it is locked (it should no longer slide).

3) Make sure that the horse's mouth contains no feed.

4) Remove the cover from the tip of the syringe.

5) Insert the syringe tip into the horse's mouth at the space between the teeth.

6) Depress the plunger as far as it will go, depositing paste on the back of the tongue.

7) Immediately raise the horse's head for a few seconds after dosing.

WARNING:

Do not use in horses intended for human consumption. Not for use in humans. Keep this and all drugs out of reach of children. Refrain from smoking and eating when handling. Wash hands after use. Avoid contact with eyes. The Safety Data Sheet (SDS) contains more detailed occupational safety information. To report adverse reactions in users, to obtain more information, or to obtain an SDS, contact Boehringer Ingelheim Animal Health USA Inc. at 1-888-637-4251.

PRECAUTIONS:

ZIMECTERIN® (ivermectin paste) has been formulated specifically for use in horses only. This product should not be used in other animal species as severe adverse reactions, including fatalities in dogs, may result.

OTHER WARNINGS:

Parasite resistance may develop to any dewormer, and has been reported for most classes of dewormers. Treatment with a dewormer used in conjunction with parasite management practices appropriate to the geographic area and the animal(s) to be treated may slow the development of parasite resistance. Fecal examinations or other diagnostic tests and parasite management history should be used to determine if the product is appropriate for the herd, prior to the use of any dewormer. Following the use of any dewormer, effectiveness of treatment should be monitored (for example, with the use of a fecal egg count reduction test or another appropriate method).

A decrease in a drug's effectiveness over time as calculated by fecal egg count reduction tests may indicate the development of resistance to the dewormer administered. Your parasite management plan should be adjusted accordingly based on regular monitoring.

ENVIRONMENTAL SAFETY:

Ivermectin and excreted ivermectin residues may adversely affect aquatic organisms. Do not contaminate ground or surface water. Dispose of the syringe in an approved landfill or by incineration.

INFORMATION FOR HORSE OWNERS:

Swelling and itching reactions after treatment with ZIMECTERIN® (ivermectin paste) have occurred in horses carrying heavy infections of neck threadworm (Onchocerca sp.) microfilariae. These reactions were most likely the result of microfilariae dying in large numbers. Symptomatic treatment may be advisable. Consult your veterinarian should any such reactions occur. Healing of summer sores involving extensive tissue changes may require other appropriate therapy in conjunction with treatment with ZIMECTERIN®. Reinfection, and measures for its prevention, should also be considered. Consult your veterinarian if the condition does not improve.

Product 7096101

® ZIMECTERIN is a registered trademark of the Boehringer Ingelheim Group.
© 2019 Boehringer Ingelheim Animal Health USA Inc.
All Rights Reserved.

Approved by FDA under NADA # 134-314

Marketed by: Boehringer Ingelheim Animal Health USA Inc. Duluth, GA, 30096

Made in Brazil

SEALED FOR SECURITY.
IF BROKEN, DO NOT ACCEPT

PRINCIPAL DISPLAY PANEL - 6.08 g Syringe Carton

ZIMECTERIN®
(ivermectin paste) 1.87%
ANTHELMINTIC AND BOTICIDE

CONTENTS WILL TREAT UP TO 1250 lb BODY WEIGHT.

Removes worms and bots with a single dose.

For Oral Use in Horses Only

Approved by FDA under NADA # 134-314

Net Wt. 0.21 oz (6.08 g)

Make every does count.
See New Instructions.